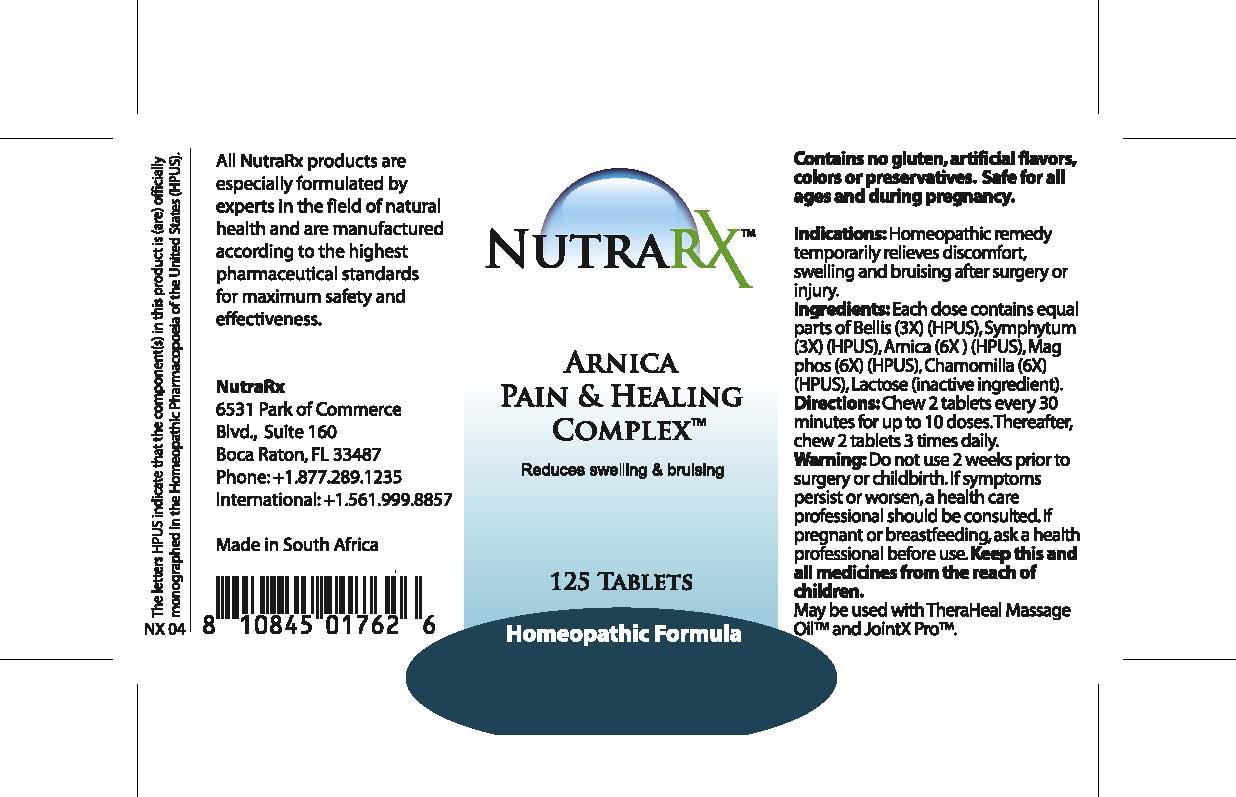 DRUG LABEL: Nutra RX Arnica Pain and Healing 
								
NDC: 68647-192 | Form: TABLET
Manufacturer: Feelgood Health
Category: homeopathic | Type: HUMAN OTC DRUG LABEL
Date: 20100922

ACTIVE INGREDIENTS: BELLIS PERENNIS 3 [hp_X]/1 1; COMFREY ROOT 3 [hp_X]/1 1; ARNICA MONTANA 6 [hp_X]/1 1; MAGNESIUM PHOSPHATE 6 [hp_X]/1 1; MATRICARIA RECUTITA 6 [hp_X]/1 1
INACTIVE INGREDIENTS: LACTOSE

NUTRARX ARNICA AND PAIN

PURPOSE

Reduces swelling and bruising

INDICATIONS AND USAGE

Indications: Homeopathic remedy temporarily relieves discomfort, swelling and bruising after surgery or injury.

DOSAGE AND ADMINISTRATION

Directions: Chew 2 tablets every 30 minutes for up to 10 doses. Thereafter, chew 2 tablets 3 times daily.

GENERAL PRECAUTIONS

Warning: Do not use 2 weeks prior to surgery or childbirth. If symptoms persist or worsen, a health care professional should be consulted. Keep this and all medicines from the reach of children.

ACTIVE INGREDIENT

Ingredients: Each dose contains equal parts of Bellis (3X) (HPUS), Symphytum (3X) (HPUS), Arnica (6X) (HPUS), Mag phos (6X) (HPUS), Chamomilla (6X) (HPUS)

Lactose (inactive ingredient).

PREGNANCY

If pregnant or breastfeeding, ask a health professional before use.

WARNINGS

Contains no gluten, artificial flavors, colors or preservatives.Safe for all ages and during pregnancy.

PATIENT COUNSELING INFORMATION

All NutraRx products are especially formulated by experts in the field of natural health and are manufactured according to the highest pharmaceutical standards for maximum safety and effectiveness.

NutraRx

6531 Park of Commerce

Blvd., Suite 160

Boca Raton, FL 33487

Phone: +1.877.289.1235

International: +1.561.999.8857

Made in South Africa

The letters HPUS indicate that the component(s) in this product is (are) officially monographed in the Homeopathic Pharmacopoeia of the United States (HPUS).

KEEP OUT OF REACH OF CHILDREN

Keep this and all medicines from the reach of children.